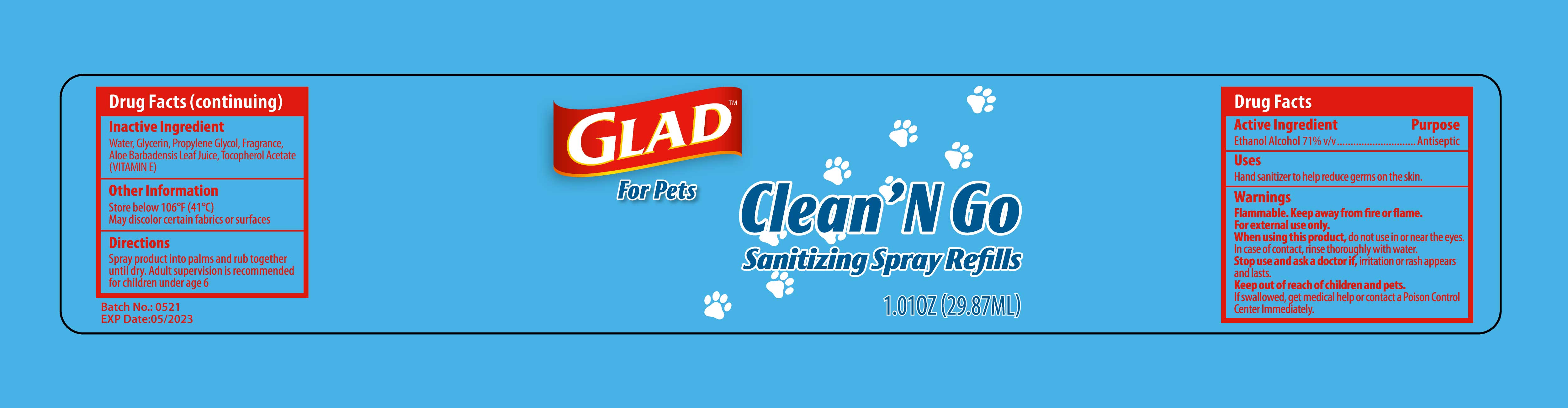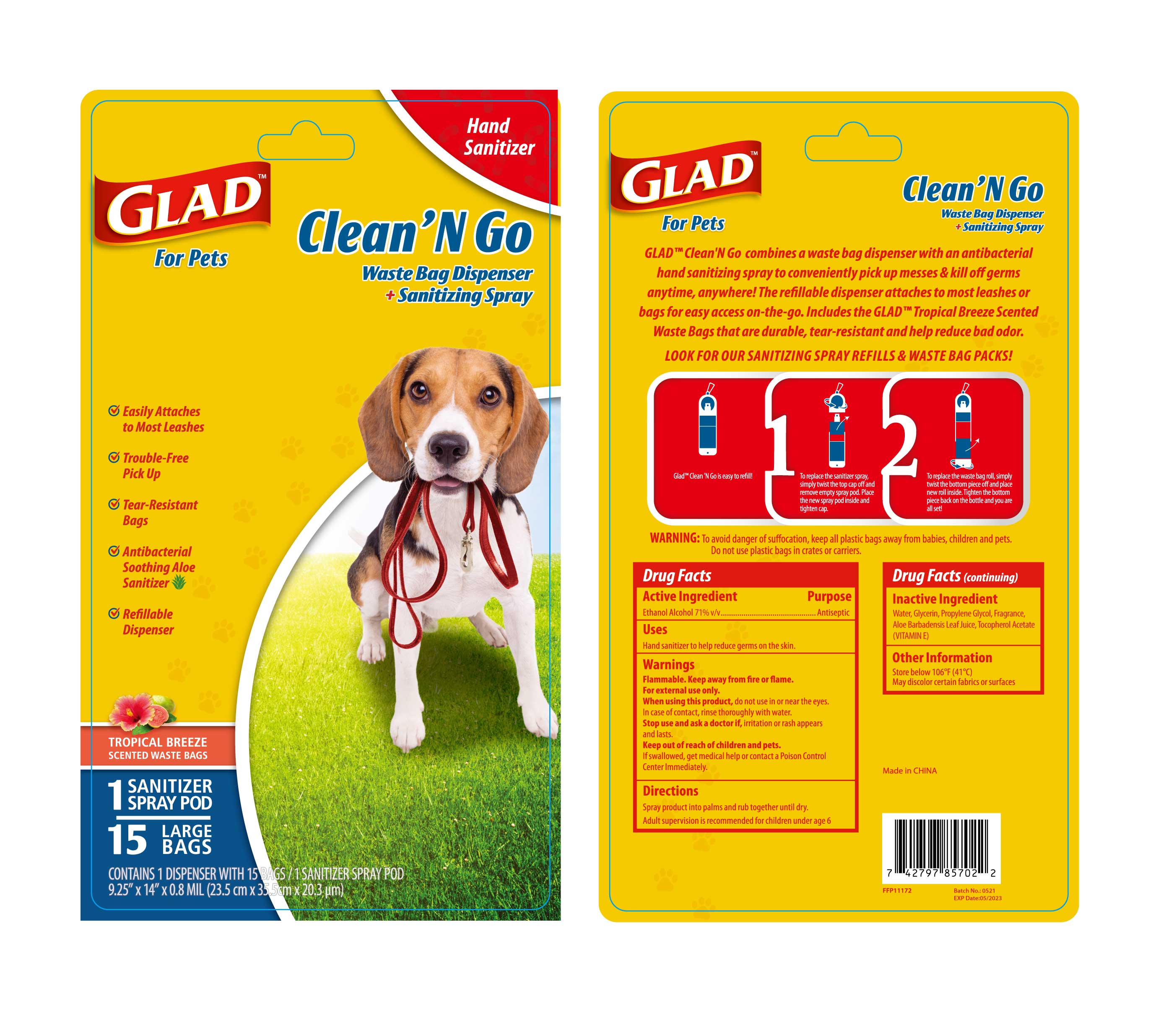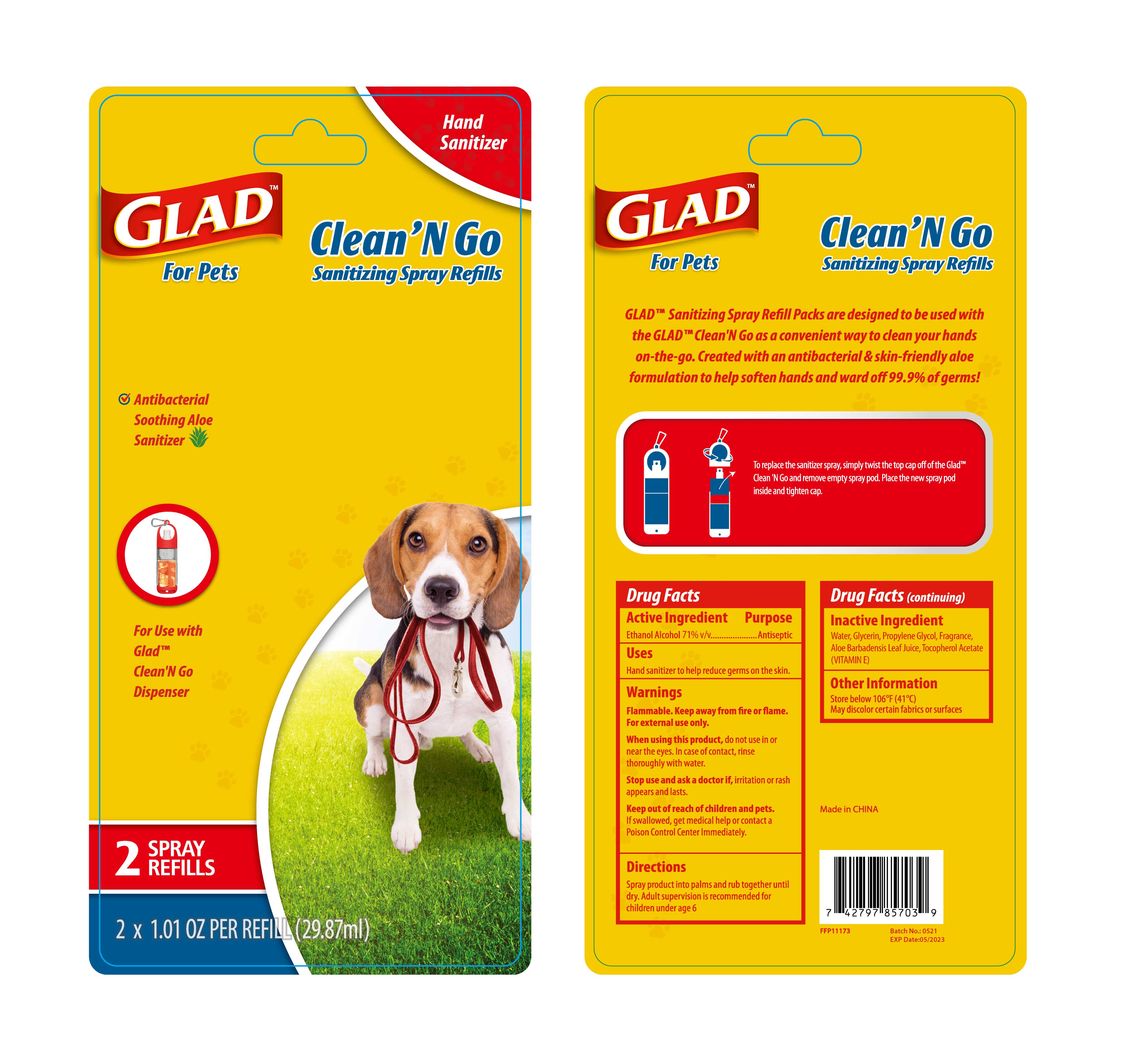 DRUG LABEL: HAND SANITIZER
NDC: 47993-330 | Form: GEL
Manufacturer: NINGBO JIANGBEI OCEAN STAR TRADING CO.,LTD
Category: otc | Type: HUMAN OTC DRUG LABEL
Date: 20220807

ACTIVE INGREDIENTS: ALCOHOL 71 mL/100 mL
INACTIVE INGREDIENTS: WATER; GLYCERIN; PROPYLENE GLYCOL; ALOE VERA LEAF; TOCOPHEROL

47993-330

Active ingredients
Ethanol Alcohol 71% v/v

PURPOSE

Antiseptic

Uses：

Hand sanitizer to help reduce germs on the skin.

Warnings:

Flammable. Keep away from fire or flame.

For external use only.

When using this product, do not use in or near the eyes. In case of contact, rinse thoroughly with water.

Stop use and ask a doctor if, irritation or rash appears and lasts.

Keep out of reach of children and pets.

If swallowed, get medical help or contact a Poison Control Center Immediately.

Inactive Ingredients

Water,Glycerin,Propylene Glycol,Fragrance,Aloe Barbadensis Leaf Juice,Tocopherol Acetate(VITAMIN E)

Other information

Store below 106℉(41℃)

May discolor certain fabrics or surfaces

Directions

Spray product into palms and rub together until dry.

Adult supervision is recommended for children under age 6.